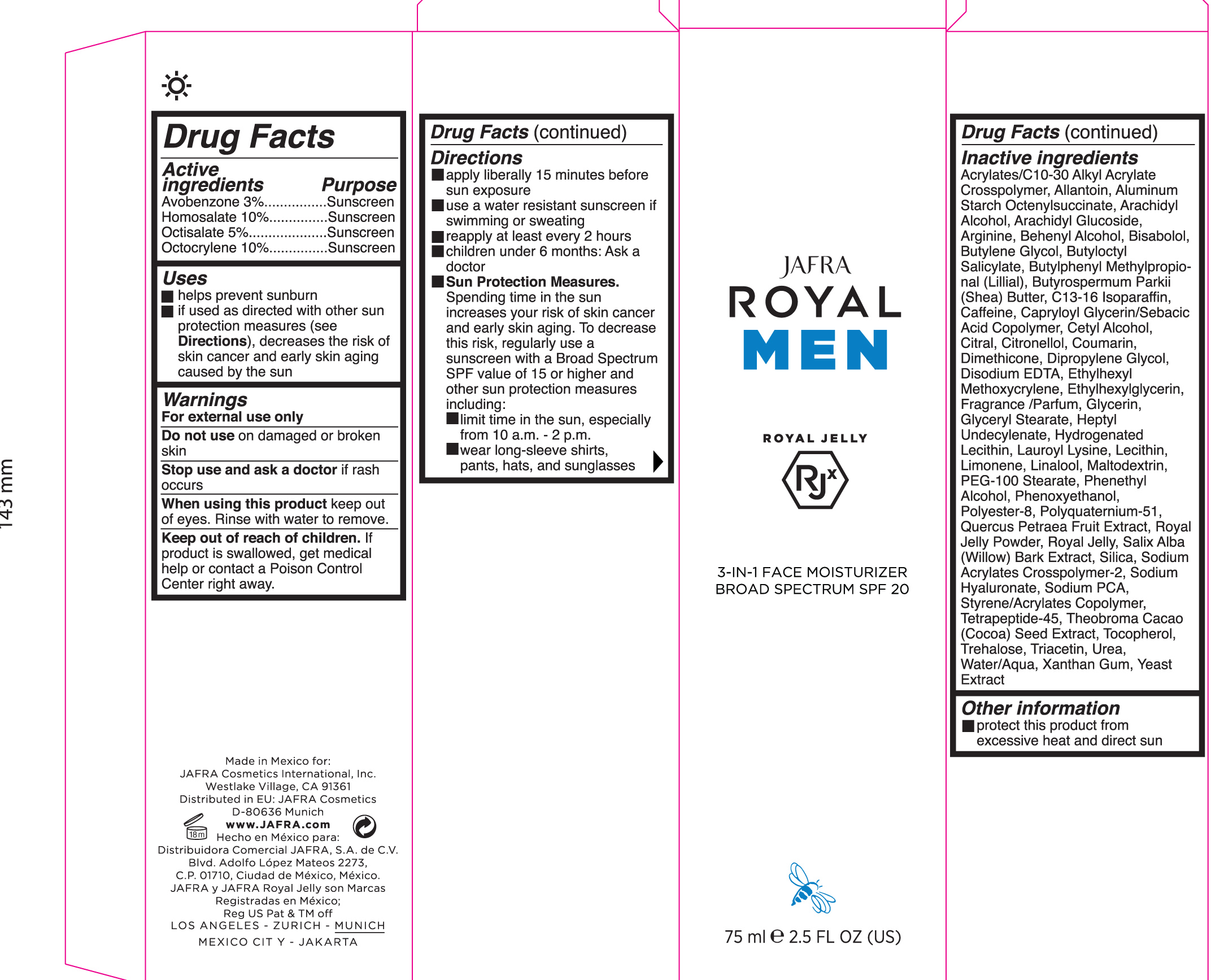 DRUG LABEL: 3-in-1 Face Moisturizer Broad Spectrum SPF 20
NDC: 68828-283 | Form: JELLY
Manufacturer: Jafra cosmetics International
Category: otc | Type: HUMAN OTC DRUG LABEL
Date: 20190327

ACTIVE INGREDIENTS: AVOBENZONE 3 g/100 mL; OCTOCRYLENE 10 g/100 mL; HOMOSALATE 10 g/100 mL; OCTISALATE 5 g/100 mL
INACTIVE INGREDIENTS: ROYAL JELLY; SALIX ALBA BARK; UREA; DOCOSANOL; LEVOMENOL; BUTYLOCTYL SALICYLATE; SHEA BUTTER; LECITHIN, SOYBEAN; LIMONENE, (+)-; MALTODEXTRIN; PHENOXYETHANOL; TRIACETIN; CARBOMER COPOLYMER TYPE A (ALLYL PENTAERYTHRITOL CROSSLINKED); ALLANTOIN, (+)-; ARACHIDYL ALCOHOL; C13-16 ISOPARAFFIN; CAPRYLOYL GLYCERIN/SEBACIC ACID COPOLYMER (2000 MPA.S); CETYL ALCOHOL; DIMETHICONE; DIPROPYLENE GLYCOL; EDETATE DISODIUM; GLYCERYL MONOSTEARATE; HYDROGENATED SOYBEAN LECITHIN; LAUROYL LYSINE; PHENYLETHYL ALCOHOL; POLYESTER-8 (1400 MW, CYANODIPHENYLPROPENOYL CAPPED); POLYQUATERNIUM-51 (2-METHACRYLOYLOXYETHYL PHOSPHORYLCHOLINE/N-BUTYL METHACRYLATE; 3:7); WATER; XANTHAN GUM; YEAST, UNSPECIFIED; CAFFEINE; CITRAL; .BETA.-CITRONELLOL, (R)-; ETHYLHEXYLGLYCERIN; GLYCERIN; COCOA; TOCOPHEROL; ALUMINUM STARCH OCTENYLSUCCINATE; BUTYLENE GLYCOL; BUTYLPHENYL METHYLPROPIONAL; HEPTYL UNDECYLENATE; PEG-100 STEARATE; SILICON DIOXIDE; COUMARIN; ETHYLHEXYL METHOXYCRYLENE; LINALOOL, (+/-)-; SODIUM PYRROLIDONE CARBOXYLATE; ARACHIDYL GLUCOSIDE; ARGININE; HYALURONATE SODIUM; TREHALOSE

3-in-1 Face Moisturizer Broad Spectrum SPF 20

Active ingredient Purpose

Avobenzone 3% Sunscreen

Homosalate 10% Sunscreen

Octisalate 5% Sunscreen

Octocrylene 10% Sunscreen

Uses

Helps Prevent Sunburn
If used as directed with other sun protection measures (see Directions), decreases the risk of skin cancer and early skin aging caused by the sun.

Keep out of reach of children

If product is swallowed, get medical help or contact a poison Control Center right away

Warnings

For external use only

Do not use on damaged or broken skin

When using this product keep out of eyes. Rinse with water to remove

Stop use and ask a doctor if

rash occurs or irritation develops and lasts.

Directions

- Apply liberally 15 minutes before sun exposure
- Use a water resistant sunscreen if swimming or sweating
- reapply at leastevery 2 hours.
- Children under 6 months of age: ask a doctor.

• Sun Protection Measures Spending time in the sun increases your risk of
skin cancer and early skin aging. To decrease this risk, regularly use a
sunscreen with a Broad Spectrum SPF value of 15 or higher and other sun
protection measures including:

- limit your time in the sun, especially from 10 a.m. – 2 p.m.
- wear long-sleeved shirts, pants, hats, and sunglasses

INACTIVE INGREDIENT

Inactive ingredients: Acrylates/C10-30 Alkyl Acrylate Crosspolymer, Allantoin, Aluminum Starch Octenylsuccinate, Arachidyl
Alcohol, Arachidyl Glucoside, Arginine, Behenyl Alcohol, Blsabolol, Butylene Glycol, Butyloctyl Salicylate, Butylphenyl Methylpropional (LIIIIal), Butyrospanmum Parkll (Shea) Butter, C13-16 Isoparaffin, Caffeine, Capryloyl Glycerin/Sabacic Acid Copolymer, Cetyl Alcohol, citral, citronellol, Coumarin, Dimethicone, Dipropylene Glycol, Disodium EDTA, Ethylhexyl Methoxycrylene, Ethylhexylglycerin, Fragrance/Parfum, Glycerin, Glyceryl Stearate, Heptyl Undecylenate, Hydrogenated Lecithin, Lauroyl Lysine, Lecithin, Limonene, Linalool, Maltodextrin, PEG-100 Stearate, Phenethyl Alcohol, Phenoxyethanol, Polyester-8, Polyquatemlum-51, Quercus Petraea Fruit Extract, Royal Jelly Powder, Royal Jelly, Salix Alba (Willow) Bark Extract, Silica, Sodium Acrylates Crosspolymer-2, Sodium Hyaluronate, Sodium PCA, Styrene/Acrylates Copolymer, Tetrapeptide-45, Theobroma Cacao (Cocoa) Seed Extract, Tocopherol, Trehalose, Triacetin, Urea, Water/Aqua, Xanthan Gum, Yeast Extract

PACKAGE LABEL

Jafra Royal Men

Royal Jelly

3-in-1 Face Moisturizer Broad Spectrum SPF 20

75 ml 2.5 Fl Oz